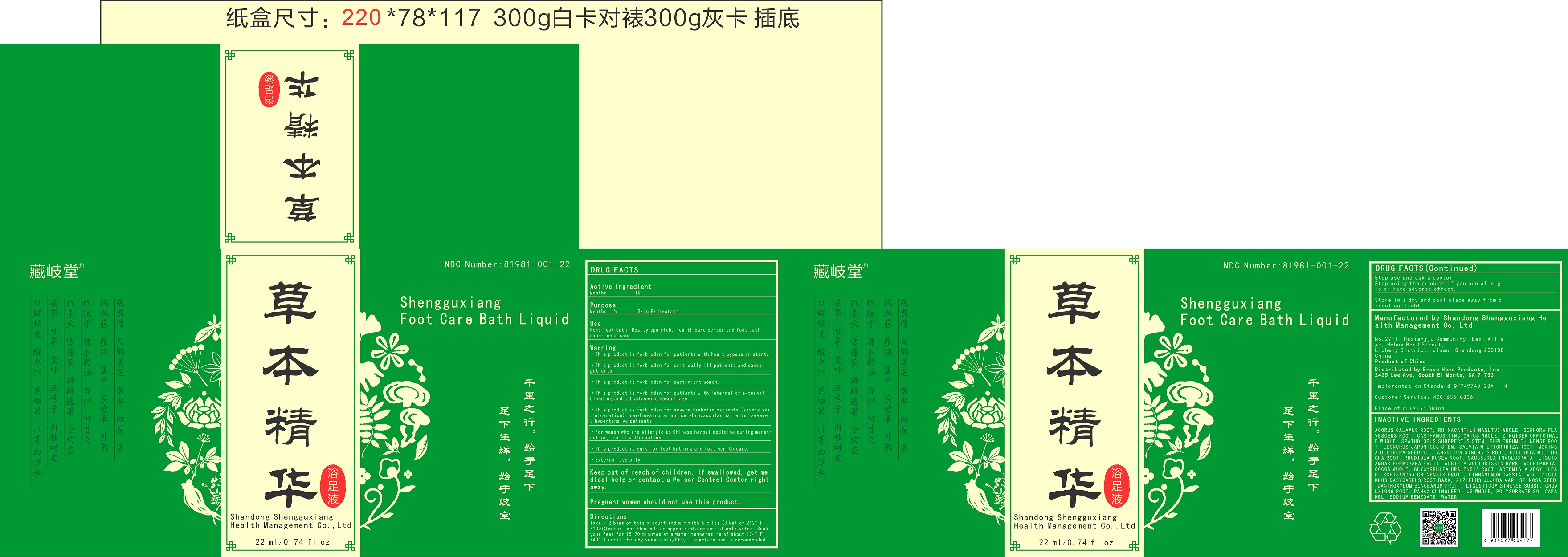 DRUG LABEL: Shengguxiang Foot Care Bath Liquid
NDC: 81981-001 | Form: LIQUID
Manufacturer: Shandong Shengguxiang Health Management Co., Ltd
Category: otc | Type: HUMAN OTC DRUG LABEL
Date: 20211019

ACTIVE INGREDIENTS: MENTHOL 1 g/100 mL
INACTIVE INGREDIENTS: ACORUS CALAMUS ROOT; RHINACANTHUS NASUTUS WHOLE; SOPHORA FLAVESCENS ROOT; CARTHAMUS TINCTORIUS WHOLE; ZINGIBER OFFICINALE WHOLE; SPATHOLOBUS SUBERECTUS STEM; BUPLEURUM CHINENSE ROOT; LEONURUS JAPONICUS STEM; SALVIA MILTIORRHIZA ROOT; MORINGA OLEIFERA SEED OIL; ANGELICA SINENSIS ROOT; FALLOPIA MULTIFLORA ROOT; RHODIOLA ROSEA ROOT; SAUSSUREA INVOLUCRATA FLOWERING TOP; LIQUIDAMBAR FORMOSANA FRUIT; ALBIZIA JULIBRISSIN BARK; WOLFIPORIA COCOS WHOLE; GLYCYRRHIZA URALENSIS ROOT; ARTEMISIA ARGYI LEAF; SCHISANDRA CHINENSIS FRUIT; CINNAMOMUM CASSIA TWIG; DICTAMNUS DASYCARPUS ROOT BARK; ZIZIPHUS JUJUBA VAR. SPINOSA SEED; ZANTHOXYLUM BUNGEANUM FRUIT; LIGUSTICUM SINENSE SUBSP. CHUANXIONG ROOT; PANAX QUINQUEFOLIUS WHOLE; POLYSORBATE 80; CARAMEL; SODIUM BENZOATE; WATER

Shandong Shengguxiang Health Management Co., Ltd

Active Ingredient

Menthol 1%

Purpose

Menthol 1% Skin Protectant

Use

Home foot bath. Beauty spa club, health care center and foot bath experience shop.

Warning

- This product is forbidden for patients with heart bypass or stents.
- This product is forbidden for critically ill patients and cancer patients.
- This product is forbidden for parturient women.
- This product is forbidden for patients with internal or external bleeding and subcutaneous hemorrhage.
- This product is forbidden for severe diabetic patients (severe skin ulceration), cardiovascular and cerebrovascular patients, severely hypertensive patients.
- For women who are allergic to Chinese herbal medicine during menstruation, use it with caution.
- This product is only for foot bathing and foot health care.
- External use only.

Directions

Take 1-2 bags of this product and mix with 6.6 lbs (3 kg) of 212°F (100℃) water, and then add an appropriate amount of cold water. Soak your feet for 15-20 minutes at a water temperature of about 104°F (40°) until the body sweats slightly. Long-term use is recommended. .

Stop use and ask a doctor

Stop using the product if you are allergic or have adverse effect.

Manufactured by Shandong Shengguxiang Health Management Co, Ltd No.27-1, Hexiangju Community, Bazi Village, Hehua Road Street, Licheng District, Jinan, Shandong 250108, China Product of China

Distributed by Bravo Home Products, Inc
2425 Lee Ave, South El Monte, CA 91733

Inactive Ingredients

ACORUS CALAMUS ROOT, RHINACANTHUS NASUTUS WHOLE, SOPHORA FLAVESCENS ROOT, CARTHAMUS TINCTORIUS WHOLE, ZINGIBER OFFICINALE WHOLE, SPATHOLOBUS SUBERECTUS STEM, BUPLEURUM CHINENSE ROOT, LEONURUS JAPONICUS STEM, SALVIA MILTIORRHIZA ROOT, MORINGA OLEIFERA SEED OIL, ANGELICA SINENSIS ROOT, FALLOPIA MULTIFLORA ROOT, RHODIOLA ROSEA ROOT, SAUSSUREA INVOLUCRATA, LIQUIDAMBAR FORMOSANA FRUIT, ALBIZIA JULIBRISSIN BARK, WOLFIPORIA COCOS WHOLE, GLYCYRRHIZA URALENSIS ROOT, ARTEMISIA ARGYI LEAF, SCHISANDRA CHINENSIS FRUIT, CINNAMOMUM CASSIA TWIG, DICTAMNUS DASYCARPUS ROOT BARK, ZIZIPHUS JUJUBA VAR. SPINOSA SEED, ZANTHOXYLUM BUNGEANUM FRUIT, LIGUSTICUM SINENSE SUBSP. CHUANXIONG ROOT, PANAX QUINQUEFOLIUS WHOLE, POLYSORBATE 80, CARAMEL COLOR, SODIUM BENZOATE, WATER